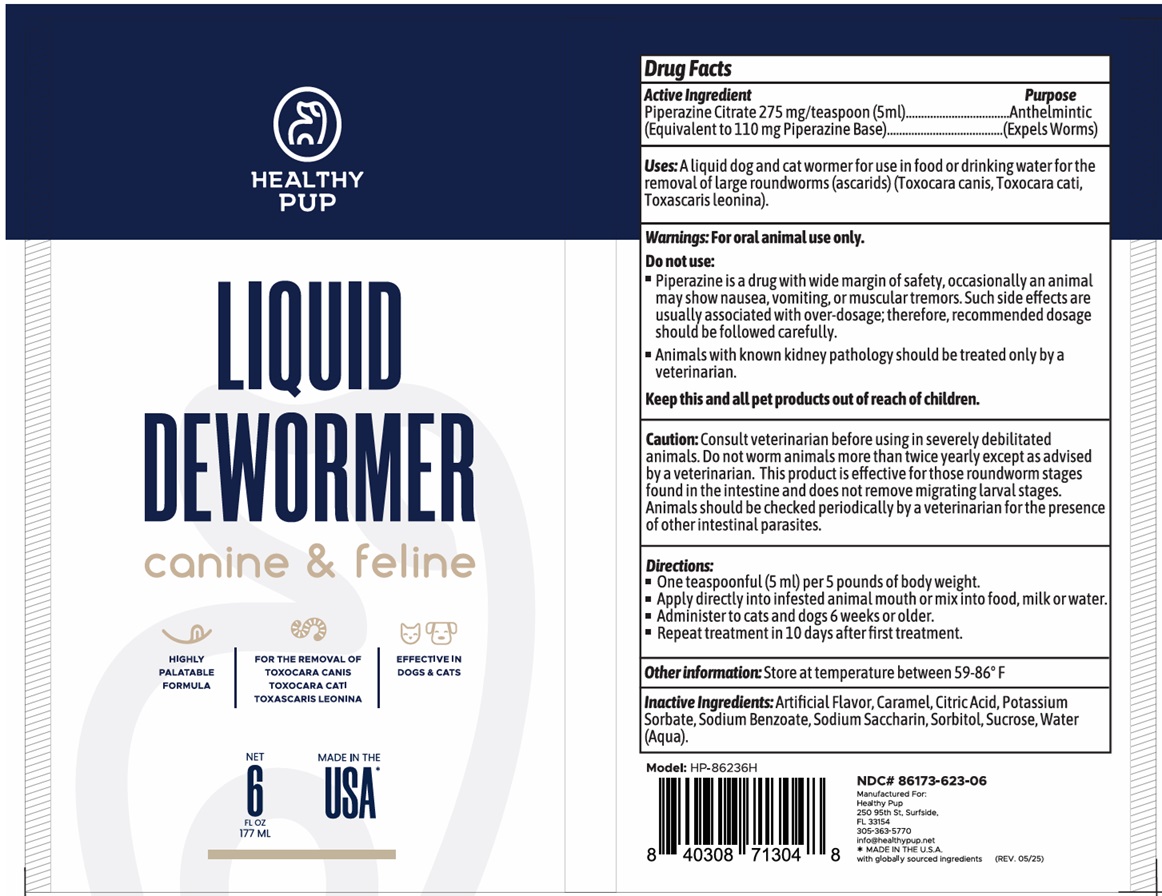 DRUG LABEL: HEALTHY PUP DEWORMER
NDC: 86173-623 | Form: LIQUID
Manufacturer: Click Industries LLC
Category: animal | Type: OTC ANIMAL DRUG LABEL
Date: 20250619

ACTIVE INGREDIENTS: PIPERAZINE CITRATE 110 mg/5 mL
INACTIVE INGREDIENTS: CARAMEL; CITRIC ACID MONOHYDRATE; POTASSIUM SORBATE; SODIUM BENZOATE; SACCHARIN SODIUM; SORBITOL; SUCROSE; WATER

HEALTHY PUP LIQUID DEWORMER

Active Ingredient

Piperazine Citrate 275 mg/teaspoon (5ml)
(Equivalent to 110 mg Piperazine Base)

Purpose

Anthelmintic
(Expels Worms)

Uses:

A liquid dog and cat wormer for use in food or drinking water for the removal of large roundworms (ascarids) (Toxocara canis, Toxocara cati, Toxascaris leonina).

Warnings:

For oral animal use only.

Do not use:
• Piperazine is a drug with wide margin of safety, occasionally an animal may show nausea, vomiting, or muscular tremors. Such side effects are usually associated with over-dosage; therefore, recommended dosage should be followed carefully.
• Animals with known kidney pathology should be treated only by a veterinarian.

KEEP OUT OF REACH OF CHILDREN

Keep this and all pet products out of reach of children.

Caution:

Consult veterinarian before using in severely debilitated animals. Do not worm animals more than twice yearly except as advised by a veterinarian. This product is effective for those roundworm stages found in the intestine and does not remove migrating larval stages. Animals should be checked periodically by a veterinarian for the presence of other intestinal parasites.

Directions:

• One teaspoonful (5 ml) per 5 pounds of body weight.
• Apply directly into infested animal mouth or mix into food, milk or water.
• Administer to cats and dogs 6 weeks or older.
• Repeat treatment in 10 days after first treatment.

Other information:

Store at temperature between 59-86o F

Inactive Ingredients:

Artificial Flavor, Caramel, Citric Acid, Potassium Sorbate, Sodium Benzoate, Sodium Saccharin, Sorbitol, Sucrose, Water (Aqua).

canine & feline

HIGHLY PALATABLE FORMULA

FOR THE REMOVAL OF
TOXOCARA CANIS
TOXOCARA CATI
TOXASCARIS LEONINA

EFFECTIVE IN DOGS & CATS

Manufactured For:
Healthy Pup
250 95th St, Surfside,
FL 33154
305-363-5770
info@healthypup.net
* MADE IN THE U.S.A.
with globally sourced ingredients